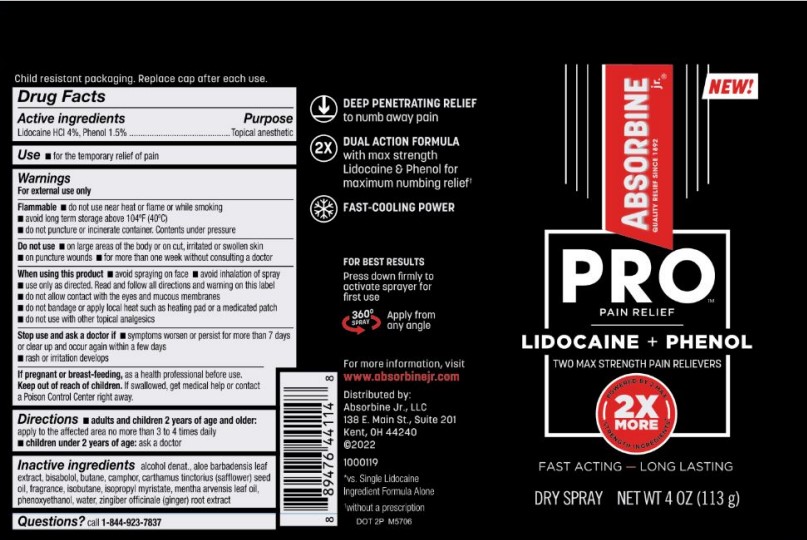 DRUG LABEL: ABSORBINE jr.
NDC: 69693-420 | Form: SPRAY
Manufacturer: Clarion Brands, LLC
Category: otc | Type: HUMAN OTC DRUG LABEL
Date: 20251223

ACTIVE INGREDIENTS: LIDOCAINE HYDROCHLORIDE 0.04 g/1 g; PHENOL 0.015 g/1 g
INACTIVE INGREDIENTS: ALCOHOL; ALOE VERA LEAF; LEVOMENOL; BUTANE; CAMPHOR OIL; SAFFLOWER OIL; ISOBUTANE; ISOPROPYL MYRISTATE; MENTHA ARVENSIS LEAF OIL; PHENOXYETHANOL; WATER; GINGER

Drug Facts

Active ingredients | Purpose
Lidocaine HCL 4%, Phenol 1.5% | Topical anesthetic

USE

- for the temporary relief of pain

Warnings

For external use only

Flammable

- do not use near heat or flame or while smoking
- avoid long term storage above 104ºF (40ºC)
- do not puncture or incinerate container. Contents under pressure

Do not use

- on large areas of the body or on cut, irritated or swollen skin
- on puncture wounds
- for more than one week without consulting a doctor

When using this product

- avoid spraying on face
- avoid inhalation of spray
- use only as directed. Read and follow all directions and warning on this label
- do not allow contact with the eyes and mucous membranes
- do not bandage or apply local heat such as heating pad or a medicated patch
- do not use with other topical analgesics

Stop use and ask a doctor if

- symptoms worsen or persist for more than 7 days or clear up and occur again within a few days
- rash or irritation develops

PREGNANCY OR BREAST FEEDING

If pregnant or breast-feeding,ask a health professional before use.

Keep out of reach of children.If swallowed, get medical help or contact a Poison Control Center right away.

Directions

- adults and children 2 years of age and older: apply to the affected area no more than 3 to 4 times daily
- children 2 years of age: ask a doctor

INACTIVE INGREDIENT

Inactive Ingredientsalcohol denat., aloe barbadersis leaf extract, bisabolol, butane, camphor, carthamus tinctorius (safflower) seed oil, fragrance, isobutane, isopropyl myristate, mentha arvensis leaf oil, phenoxyethanol, water, zingiber offcinale (ginger) root extract

Questions?call 1-844-923-7837

PACKAGE LABEL

NEW!
ABSORBINE jr.®
PRO™
PAIN RELIEF
QUALITY RELIEF SINCE 1892
LIDOCAINE + PHENOL
TWO MAX STRENGTH PAIN RELIEVERS
2X
MORE
POWERED BY 2 MAX
STRENGTH PAIN RELIEVERS
FAST ACTING – LONG LASTING
DRY SPRAY NET WT 4 0Z (113 g)

DEEP PENETRATING RELIEF
to numb away pain
DUAL ACTION FORMULA
With max strength
Lidocaine & Phenol for
maximum numbing relief*
FAST-COOLING POWER

FOR BEST RESULTS
Press down firmly to
activate sprayer for
first use
360º SPRAY
Apply from
any angle

For more information, visit
www.absorbinejr.com
Distributed by:
Absorbine Jr, LLC
138 E. Main St., Suite 201
Kent, OH 44240
©2022
1000119
*vs. Single Lidocaine
Ingredient Formula Alone
without a prescription
DOT 2P M5706